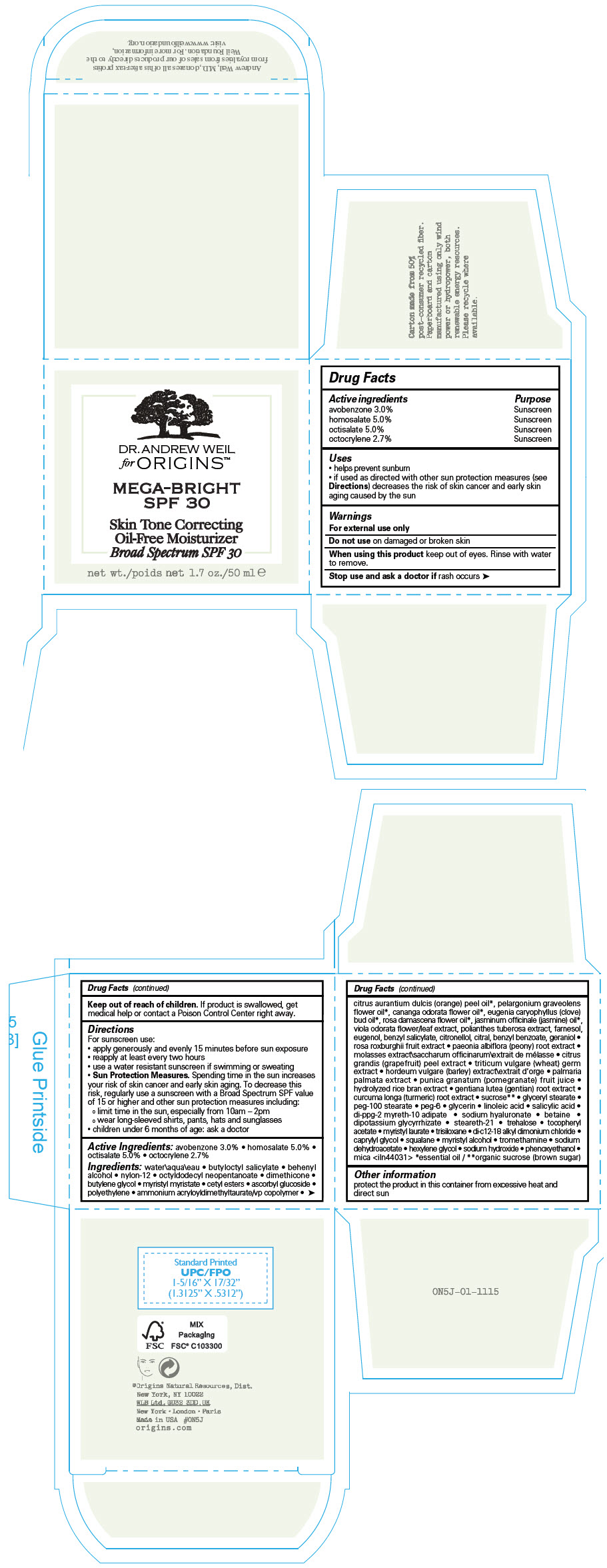 DRUG LABEL: DR. ANDREW WEIL FOR ORIGINS
NDC: 59427-112 | Form: CREAM
Manufacturer: ORIGINS NATURAL RESOURCES INC.
Category: otc | Type: HUMAN OTC DRUG LABEL
Date: 20241225

ACTIVE INGREDIENTS: HOMOSALATE 50 mg/1 mL; OCTISALATE 50 mg/1 mL; AVOBENZONE 30 mg/1 mL; OCTOCRYLENE 27 mg/1 mL
INACTIVE INGREDIENTS: WATER; BUTYLOCTYL SALICYLATE; DOCOSANOL; NYLON-12; OCTYLDODECYL NEOPENTANOATE; BUTYLENE GLYCOL; DIMETHICONE; MYRISTYL MYRISTATE; CETYL ESTERS WAX; ASCORBYL GLUCOSIDE; HIGH DENSITY POLYETHYLENE; AMMONIUM ACRYLOYLDIMETHYLTAURATE/VP COPOLYMER; ORANGE OIL, COLD PRESSED; PELARGONIUM GRAVEOLENS FLOWER OIL; YLANG-YLANG OIL; CLOVE OIL; ROSA X DAMASCENA FLOWER OIL; JASMINUM OFFICINALE FLOWER; VIOLA ODORATA FLOWERING TOP; FARNESOL; EUGENOL; BENZYL SALICYLATE; .BETA.-CITRONELLOL, (R)-; CITRAL; BENZYL BENZOATE; GERANIOL; ROSA ROXBURGHII FRUIT; PAEONIA LACTIFLORA ROOT; MOLASSES; CITRUS MAXIMA FRUIT RIND; WHEAT GERM; BARLEY; PALMARIA PALMATA; POMEGRANATE JUICE; RICE BRAN; GENTIANA LUTEA ROOT; TURMERIC; SUCROSE; GLYCERYL MONOSTEARATE; PEG-100 STEARATE; PEG-6 STEARATE; GLYCERIN; LINOLEIC ACID; SALICYLIC ACID; DI-PPG-2 MYRETH-10 ADIPATE; HYALURONATE SODIUM; BETAINE; GLYCYRRHIZINATE DIPOTASSIUM; STEARETH-21; TREHALOSE; .ALPHA.-TOCOPHEROL ACETATE; MYRISTYL LAURATE; TRISILOXANE; CAPRYLYL GLYCOL; SQUALANE; MYRISTYL ALCOHOL; TROMETHAMINE; SODIUM DEHYDROACETATE; HEXYLENE GLYCOL; SODIUM HYDROXIDE; PHENOXYETHANOL; MICA; N-DIALKYL METHYL BENZYL AMMONIUM CHLORIDE (C12-C18)

Dr. Andrew Weil for Origins™
MEGA-BRIGHT SPF 30 SKIN TONE CORRECTING OIL FREE MOISTURIZER BROAD SPECTRUM

Drug Facts

ACTIVE INGREDIENT

Active ingredients | Purpose
avobenzone 3.00% | Sunscreen
homosalate 5.00% | Sunscreen
octisalate 5.00% | Sunscreen
octocrylene 2.70% | Sunscreen

Uses

- helps prevent sunburn
- if used as directed with other sun protection measures (see Directions) decreases the risk of skin cancer and early skin aging caused by the sun

Warnings

For external use only

Do not use on damaged or broken skin

When using this product keep out of eyes. Rinse with water to remove.

Stop use and ask a doctor if rash occurs

Keep out of reach of children. If product is swallowed, get medical help or contact a Poison Control Center right away.

Directions

For sunscreen use:

- apply generously and evenly 15 minutes before sun exposure
- reapply at least every two hours
- use a water resistant sunscreen if swimming or sweating
- Sun Protection Measures. Spending time in the sun increases your risk of skin cancer and early skin aging. To decrease this risk, regularly use a sunscreen with a Broad Spectrum SPF value of 15 or higher and other sun protection measures including:
  - limit time in the sun, especially from 10am – 2pm
  - wear long-sleeved shirts, pants, hats and sunglasses
- children under 6 months of age: ask a doctor

Ingredients

water\aqua\eau • butyloctyl salicylate • behenyl alcohol • nylon-12 • octyldodecyl neopentanoate • dimethicone • butylene glycol • myristyl myristate • cetyl esters • ascorbyl glucoside • polyethylene • ammonium acryloyldimethyltaurate/vp copolymer • citrus aurantium dulcis (orange) peel oil [essential oil] , pelargonium graveolens flower oil , cananga odorata flower oil , eugenia caryophyllus (clove) bud oil , rosa damascena flower oil , jasminum officinale (jasmine) oil , viola odorata flower/leaf extract, polianthes tuberosa extract, farnesol, eugenol, benzyl salicylate, citronellol, citral, benzyl benzoate, geraniol • rosa roxburghii fruit extract • paeonia albiflora (peony) root extract • molasses extract\saccharum officinarum\extrait de mélasse • citrus grandis (grapefruit) peel extract • triticum vulgare (wheat) germ extract • hordeum vulgare (barley) extract\extrait d'orge • palmaria palmata extract • punica granatum (pomegranate) fruit juice • hydrolyzed rice bran extract • gentiana lutea (gentian) root extract • curcuma longa (turmeric) root extract • sucrose [organic sucrose (brown sugar)] • glyceryl stearate • peg-100 stearate • peg-6 • glycerin • linoleic acid • salicylic acid • di-ppg-2 myreth-10 adipate • sodium hyaluronate • betaine • dipotassium glycyrrhizate • steareth-21 • trehalose • tocopheryl acetate • myristyl laurate • trisiloxane • di-c12-18 alkyl dimonium chloride • caprylyl glycol • squalane • myristyl alcohol • tromethamine • sodium dehydroacetate • hexylene glycol • sodium hydroxide • phenoxyethanol • mica <iln44031>

Other information

protect the product in this container from excessive heat and direct sun

PRINCIPAL DISPLAY PANEL - 50 ml Jar Carton

DR. ANDREW WEIL
for ORIGINS™

MEGA-BRIGHT
SPF 30

Skin Tone Correcting
Oil-Free Moisturizer
Broad Spectrum SPF 30

net wt. 1.7 oz./50 ml e